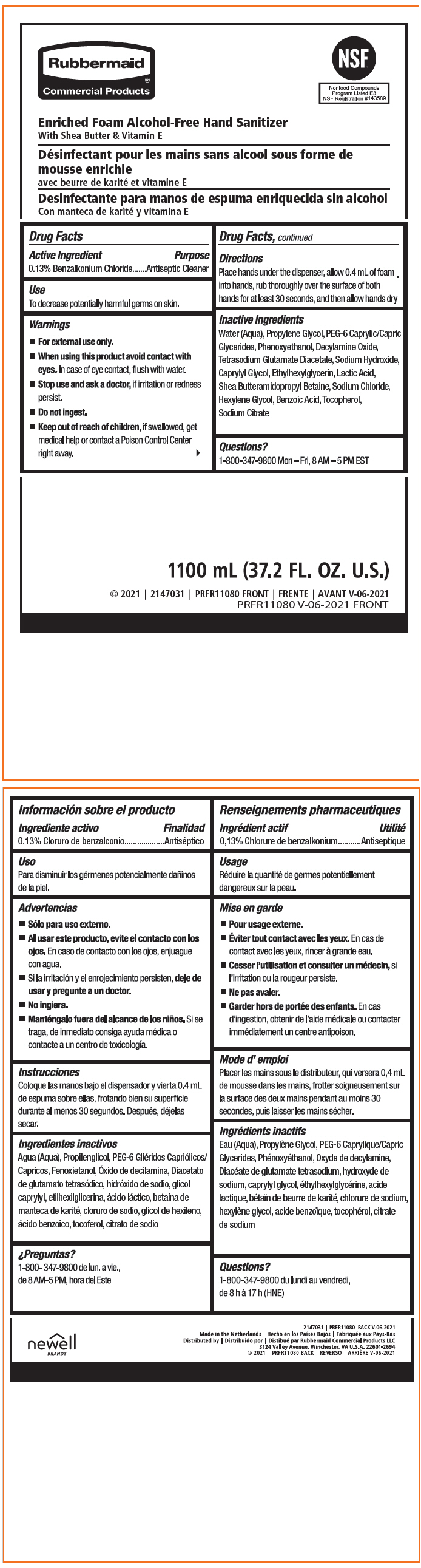 DRUG LABEL: Enriched Foam Alcohol-Free Hand Sanitizer
NDC: 65321-039 | Form: LIQUID
Manufacturer: Rubbermaid Commercial Products LLC
Category: otc | Type: HUMAN OTC DRUG LABEL
Date: 20240927

ACTIVE INGREDIENTS: BENZALKONIUM CHLORIDE 13 mg/100 mL
INACTIVE INGREDIENTS: WATER; PROPYLENE GLYCOL; CAPRYLOCAPROYL POLYOXYLGLYCERIDES 6; PHENOXYETHANOL; DECYLAMINE OXIDE; TETRASODIUM GLUTAMATE DIACETATE; SODIUM HYDROXIDE; CAPRYLYL GLYCOL; ETHYLHEXYLGLYCERIN; LACTIC ACID, UNSPECIFIED FORM; SODIUM CHLORIDE; HEXYLENE GLYCOL; BENZOIC ACID; .ALPHA.-TOCOPHEROL, D-; SODIUM CITRATE, UNSPECIFIED FORM

Enriched Foam Alcohol-Free Hand Sanitizer

Drug Facts

Active Ingredient

0.13% Benzalkonium Chloride

Purpose

Antiseptic Cleaner

Use

To decrease potentially harmful germs on skin.

Warnings

- For external use only.

- When using this product avoid contact with eyes. In case of eye contact, flush with water.

- Stop use and ask a doctor, if irritation or redness persist.

- Do not ingest.

- Keep out of reach of children, if swallowed, get medical help or contact a Poison Control Center right away.

Directions

Place hands under the dispenser, allow 0.4 mL of foam into hands, rub thoroughly over the surface of both hands for at least 30 seconds, and then allow hands dry

Inactive Ingredients

Water (Aqua), Propylene Glycol, PEG-6 Caprylic/Capric Glycerides, Phenoxyethanol, Decylamine Oxide, Tetrasodium Glutamate Diacetate, Sodium Hydroxide, Caprylyl Glycol, Ethylhexylglycerin, Lactic Acid, Shea Butteramidopropyl Betaine, Sodium Chloride, Hexylene Glycol, Benzoic Acid, Tocopherol, Sodium Citrate

Questions?

1-800-347-9800 Mon – Fri, 8 AM – 5 PM EST

Distributed by | Rubbermaid Commercial Products LLC
3124 Valley Avenue, Winchester, VA U.S.A. 22601-2694

PRINCIPAL DISPLAY PANEL - 1100 mL Pouch Label

Rubbermaid®
Commercial Products

Enriched Foam Alcohol-Free Hand Sanitizer
With Shea Butter & Vitamin E

NSF®

Nonfood Compounds
Program Listed E3
NSF Registration #143589

1100 mL (37.2 FL. OZ. U.S.)

© 2021 | 2147031 | PRFR11080 FRONT
PRFR11080 V-06-2021 FRONT